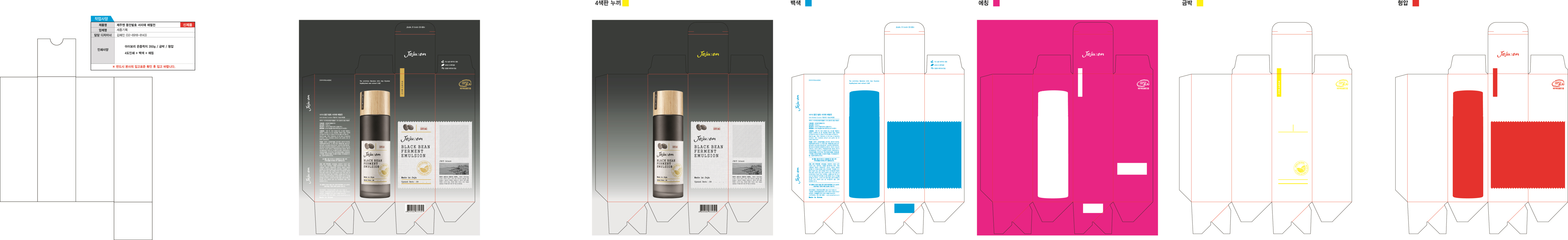 DRUG LABEL: PureHeals Centella 70 Toning Swab
NDC: 59535-0268 | Form: LIQUID
Manufacturer: AMI Cosmetic Co.,Ltd.
Category: otc | Type: HUMAN OTC DRUG LABEL
Date: 20170701

ACTIVE INGREDIENTS: GLYCERIN 1 g/100 mL
INACTIVE INGREDIENTS: WATER; BUTYLENE GLYCOL

Drug Facts

ACTIVE INGREDIENT

Adenosine

INACTIVE INGREDIENT

Water, Glycerin, Butylene Glycol, Etc

PURPOSE

Skin Protectant - Anti Wrinkle

keep out of reach of the children

INDICATIONS AND USAGE

After face wash, apply proper amount of toner appropriately to the skin at the emulsion stage.

Spread it evenly across the face and gently tap them for easy absorption.

WARNINGS

1. Do not use in the following cases(Eczema and scalp wounds)
2.Side Effects
1)Due to the use of this druf if rash, irritation, itching and symptopms of hypersnesitivity occur dicontinue use and consult your phamacisr or doctor
3.General Precautions
1)If in contact with the eyes, wash out thoroughty with water If the symptoms are servere, seek medical advice immediately
2)This product is for exeternal use only. Do not use for internal use
4.Storage and handling precautions
1)If possible, avoid direct sunlight and store in cool and area of low humidity
2)In order to maintain the quality of the product and avoid misuse
3)Avoid placing the product near fire and store out in reach of children

DOSAGE AND ADMINISTRATION

for external use only